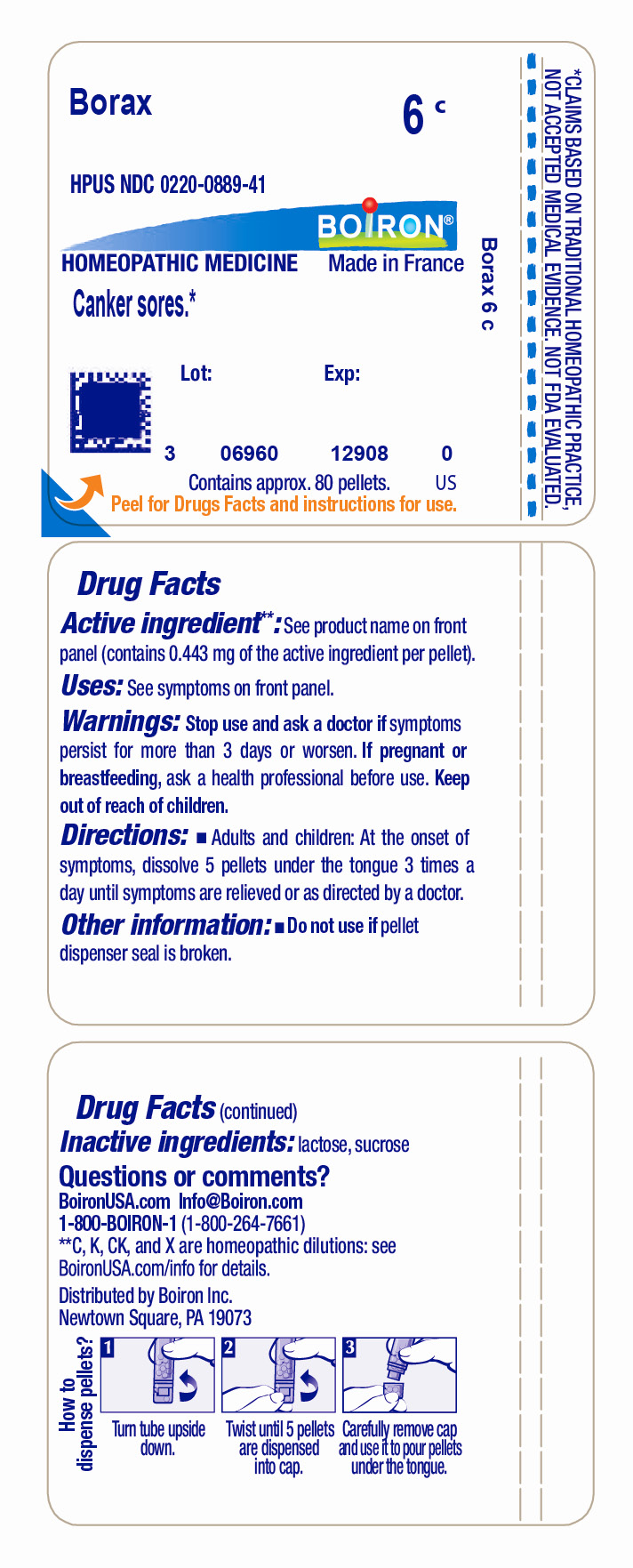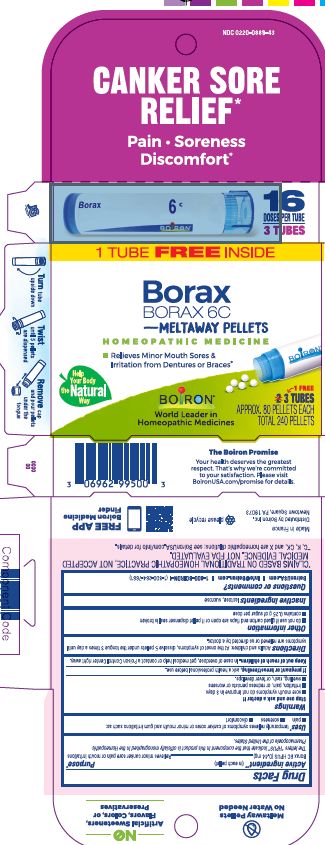 DRUG LABEL: Borax
NDC: 0220-0889 | Form: PELLET
Manufacturer: Boiron
Category: homeopathic | Type: HUMAN OTC DRUG LABEL
Date: 20230123

ACTIVE INGREDIENTS: SODIUM BORATE 6 [hp_C]/6 [hp_C]
INACTIVE INGREDIENTS: SUCROSE; LACTOSE, UNSPECIFIED FORM

Borax 6C

Active ingedient** (in each pellet)

Borax 6C HPUS (0.44 mg)

The letters "HPUS" indicate that the component in this product is offically monographed in the Homeopathic Pharmacopoeia of the United States.

Purpose*

Relieves minor canker sore pain or mouth irritations

Uses*

temporarily relieves symptoms of canker sores or minor mouth and gum irritations such as:

- pain
- soreness
- discomfort

Tube- Canker Sores*

Stop use and ask a doctor if

- sore mouth symptoms do not improve in 3 days
- irritation, pain, or redness persists or worsens
- swelling, rash, or fever develops.

Tube- Stop use and ask a doctor if symptoms persist for more than 3 days or worsen

PREGNANCY OR BREAST FEEDING

If pregnant or breastfeeding, ask a health professional before use.

Keep out of reach of children. In case overdose, get medical help or contact a Poison Control Center right away.

DOSAGE AND ADMINISTRATION

Adults and children: At the onset of symptoms, dissolve 5 pellets under the tongue 3 times a day until symptoms are relieved or as directed by a doctor.

- do not use if glued carton end flaps are open or if pellet dispenser seal is broken
- contains 0.25 g of sugar per dose

Canker Sore Relief*

Pain Soreness Discomfort*

3 TUBES

APPROX. 80 PELLETS EACH

TOTAL 240 PELLETS

16 DOSES PER TUBE

Relieves Minor Sores & Irritation from Dentures or Braces*

Turn tube upside down Twist until 5 pellets are dispensed Remove cap and pour pellets under the tongue

Tube-

Do not use if pellet dispenser seal is broken.
Contains approx. 80 pellets.
How to dispense pellets? Turn tube upside down. Twist until 5 pellets are dispensed into cap. Carefully remove the cap and use it to pour pellets under the tongue.
*CLAIMS BASED ON TRADITIONAL HOMEOPATHIC PRACTICE NOT ACCEPTED MEDICAL EVIDENCE. NOT FDA EVALUATED.
*C,K,CK, and X are homeopathic dilutions: see BoironUSA.com/info for details.

INACTIVE INGREDIENT

lactose, sucrose

QUESTIONS

1-800-BOIRON-1 (1-800-264-7661),
BoironUSA.com Info@boiron.com
Distributed by Boiron, Inc. Newtown Square, PA 19073